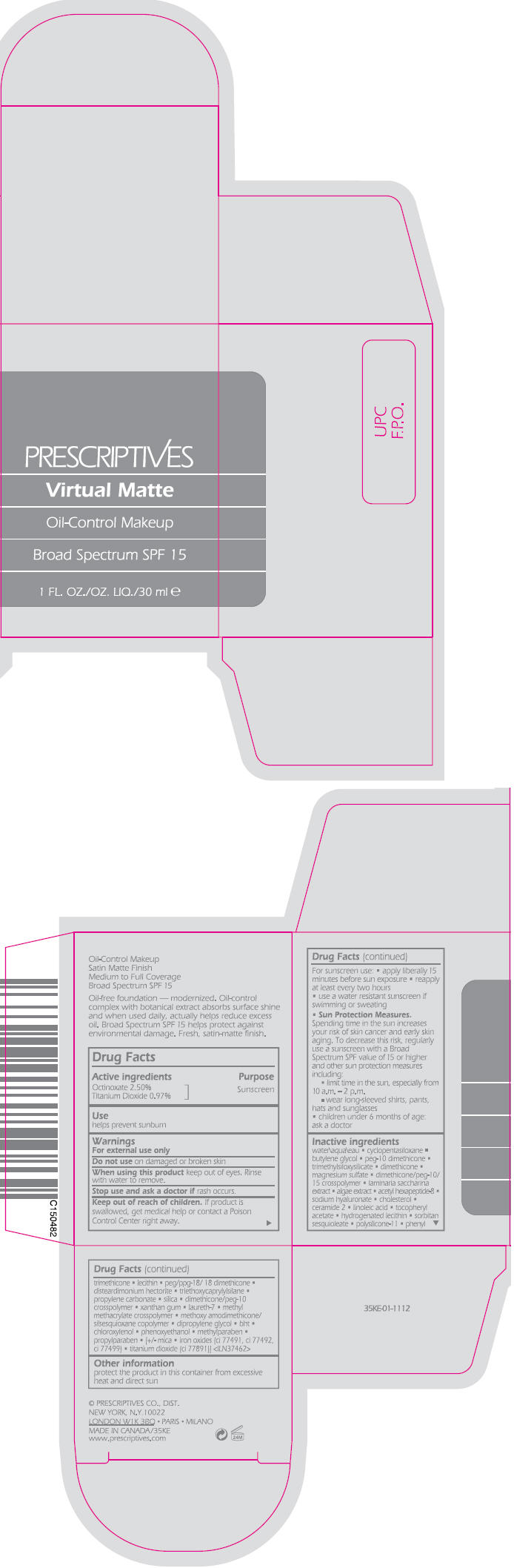 DRUG LABEL: VIRTUAL MATTE 
NDC: 59158-915 | Form: LIQUID
Manufacturer: PRESCRIPTIVES INC
Category: otc | Type: HUMAN OTC DRUG LABEL
Date: 20130618

ACTIVE INGREDIENTS: OCTINOXATE 0.02775 g/1 mL; TITANIUM DIOXIDE 0.010767 g/1 mL
INACTIVE INGREDIENTS: Water; cyclomethicone 5; butylene glycol; dimethicone; magnesium sulfate; saccharina latissima; acetyl hexapeptide-8; hyaluronate sodium; cholesterol; ceramide 2; linoleic acid; .alpha.-tocopherol acetate; sorbitan sesquioleate; phenyl trimethicone; peg/ppg-18/18 dimethicone; disteardimonium hectorite; triethoxycaprylylsilane; propylene carbonate; silicon dioxide; xanthan gum; laureth-7; dipropylene glycol; butylated hydroxytoluene; chloroxylenol; phenoxyethanol; methylparaben; propylparaben; mica; FERRIC OXIDE RED; FERRIC OXIDE YELLOW; FERROSOFERRIC OXIDE

VIRTUAL MATTE
OIL CONTROL MAKEUP BROAD SPECTRUM SPF 15

Drug Facts

Active ingredients

Octinoxate 2.50%
Titanium Dioxide 0.97%

Purpose

Sunscreen

Use

helps prevent sunburn

Warnings

For external use only

Do not use on damaged or broken skin

When using this product keep out of eyes. Rinse with water to remove.

Stop use and ask a doctor if rash occurs.

Keep out of reach of children. If product is swallowed, get medical help or contact a Poison Control Center right away.

For sunscreen use:

- apply liberally 15 minutes before sun exposure
- reapply at least every two hours
- use a water resistant sunscreen if swimming or sweating
- Sun Protection Measures. Spending time in the sun increases your risk of skin cancer and early skin aging. To decrease this risk, regularly use a sunscreen with a Broad Spectrum SPF value of 15 or higher and other sun protection measures including:
  - limit time in the sun, especially from 10 a.m. – 2 p.m.
  - wear long-sleeved shirts, pants, hats and sunglasses
- children under 6 months of age: ask a doctor

Inactive ingredients

water\aqua\eau • cyclopentasiloxane • butylene glycol • peg-10 dimethicone • trimethylsiloxysilicate • dimethicone • magnesium sulfate • dimethicone/peg-10/15 crosspolymer • laminaria saccharina extract • algae extract • acetyl hexapeptide-8 • sodium hyaluronate • cholesterol • ceramide 2 • linoleic acid • tocopheryl • acetate • hydrogenated lecithin • sorbitan sesquioleate • polysilicone-11 • phenyl trimethicone • lecithin • peg/ppg-18/ 18 dimethicone • disteardimonium hectorite • triethoxycaprylylsilane • propylene carbonate • silica • dimethicone/peg-10 crosspolymer • xanthan gum • laureth-7 • methyl methacrylate crosspolymer • methoxy amodimethicone/ silsesquioxane copolymer • dipropylene glycol • bht • chloroxylenol • phenoxyethanol • methylparaben • propylparaben • [+/- mica • iron oxides (ci 77491, ci 77492, ci 77499) • titanium dioxide (ci 77891)] <ILN37462>

Other information

protect the product in this container from excessive heat and direct sun

PRINCIPAL DISPLAY PANEL - 30 mL Bottle Carton

PRESCRIPTIVES

Virtual Matte

Oil-Control Makeup

Broad Spectrum SPF 15

1 FL. OZ./OZ. LIQ./30 ml e